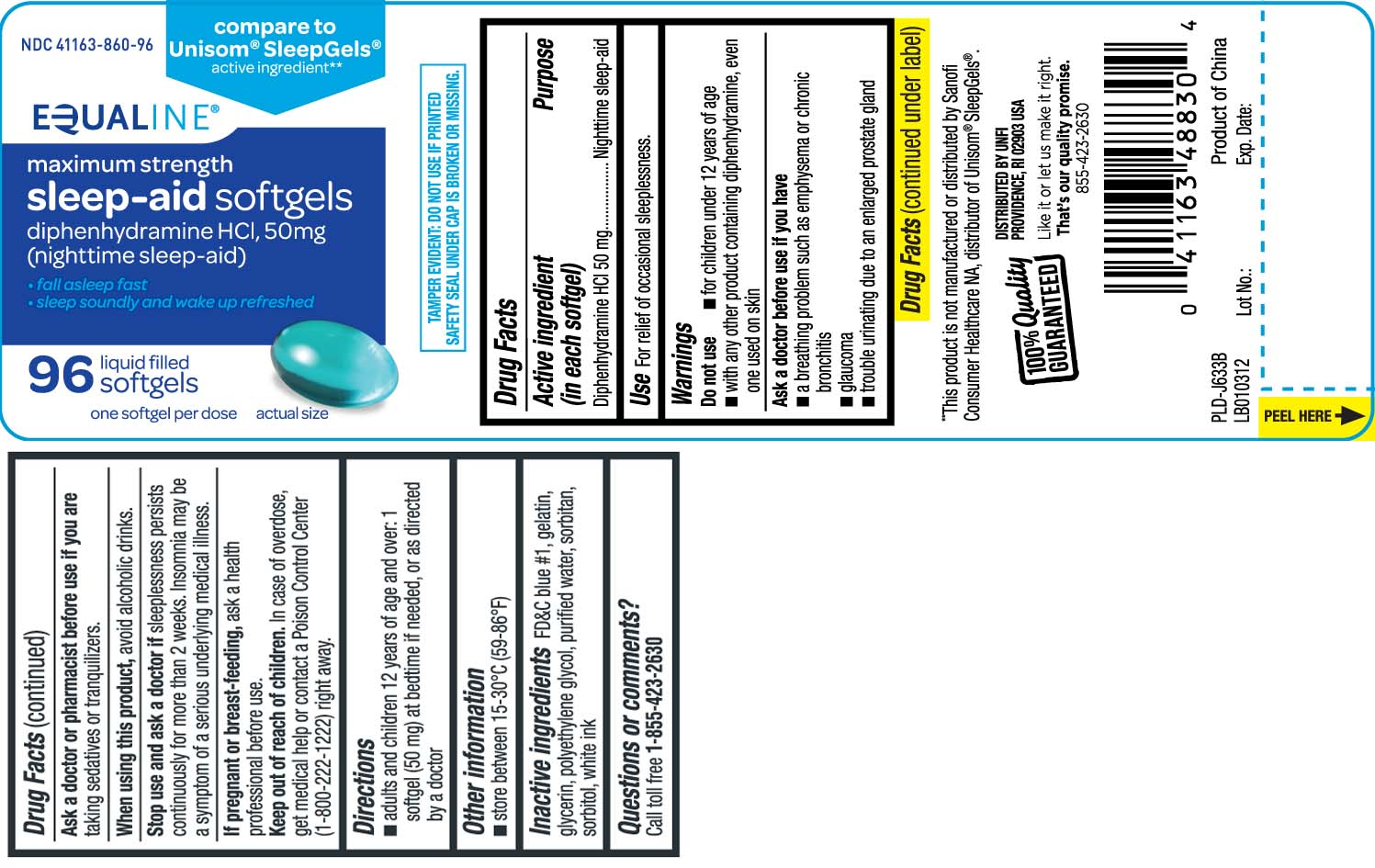 DRUG LABEL: Sleep Aid
NDC: 41163-860 | Form: CAPSULE
Manufacturer: United Natural Foods, Inc. dba UNFI
Category: otc | Type: HUMAN OTC DRUG LABEL
Date: 20250421

ACTIVE INGREDIENTS: DIPHENHYDRAMINE HYDROCHLORIDE 50 mg/1 1
INACTIVE INGREDIENTS: FD&C BLUE NO. 1; GELATIN; GLYCERIN; POLYETHYLENE GLYCOL, UNSPECIFIED; WATER; SORBITOL; SORBITAN

Drug Facts

Active ingredient (in each softgel)

Diphenhydramine HCl 50 mg

Purpose

Nighttime sleep-aid

Uses

For relief of occasional sleeplessness.

Warnings

Do not use

- for children under 12 years of age
- with any other product containing diphenhydramine, even one used on skin

Ask a doctor before use if you have

- a breathing problem such as emphysema or chronic bronchitis
- glaucoma
- trouble urinating due to an enlarged prostate gland

Ask a doctor or pharmacist before use if you are

taking sedatives or tranquilizers.

When using this product

- avoid alcoholic drinks

Stop use and ask a doctor if

sleeplessness persists continuously for more than 2 weeks. Insomnia may be a symptom of a serious underlying medical illness.

If pregnant or breast-feeding,

ask a health professional before use.

Keep out of reach of children.

In case of overdose, get medical help or contact a Poison Control Center (1-800-222-1222) right away.

Directions

- adults and children 12 years of age and older: 1 softgel (50 mg) at bedtime if needed, or as directed by a doctor

Other information

- store between 15-30ºC (59-86ºF)

Inactive ingredients

FD&C blue #1, gelatin, glycerin, polyethylene glycol, purified water, sorbitol, sorbitan, white ink

Questions or comments?

Call toll free 1-855-423-2630

Principal Display Panel

Compare to Unisom® SleepGels® active ingredient**

maximum strength

Sleep-Aid softgels

diphenhydramine HCl, 50 mg

(nighttime Sleep-Aid)

- Fall asleep fast
- sleep soundly and wake up refreshed

liquid filled

softgels

one softgel per dose

**This product is not manufactured or distributed by Sanofi Consumer Healthcare NA, distributor of Unisom® SleepGels®.

TAMPER EVIDENT: DO NOT USE IF PRINTED SAFETY SEAL UNDER CAP IS BROKEN OR MISSING.

DISTRIBUTED BY UNFI

PROVIDENCE, RI 02908 USA

Product Label

EQUALINE Nighttime Sleep-Aid